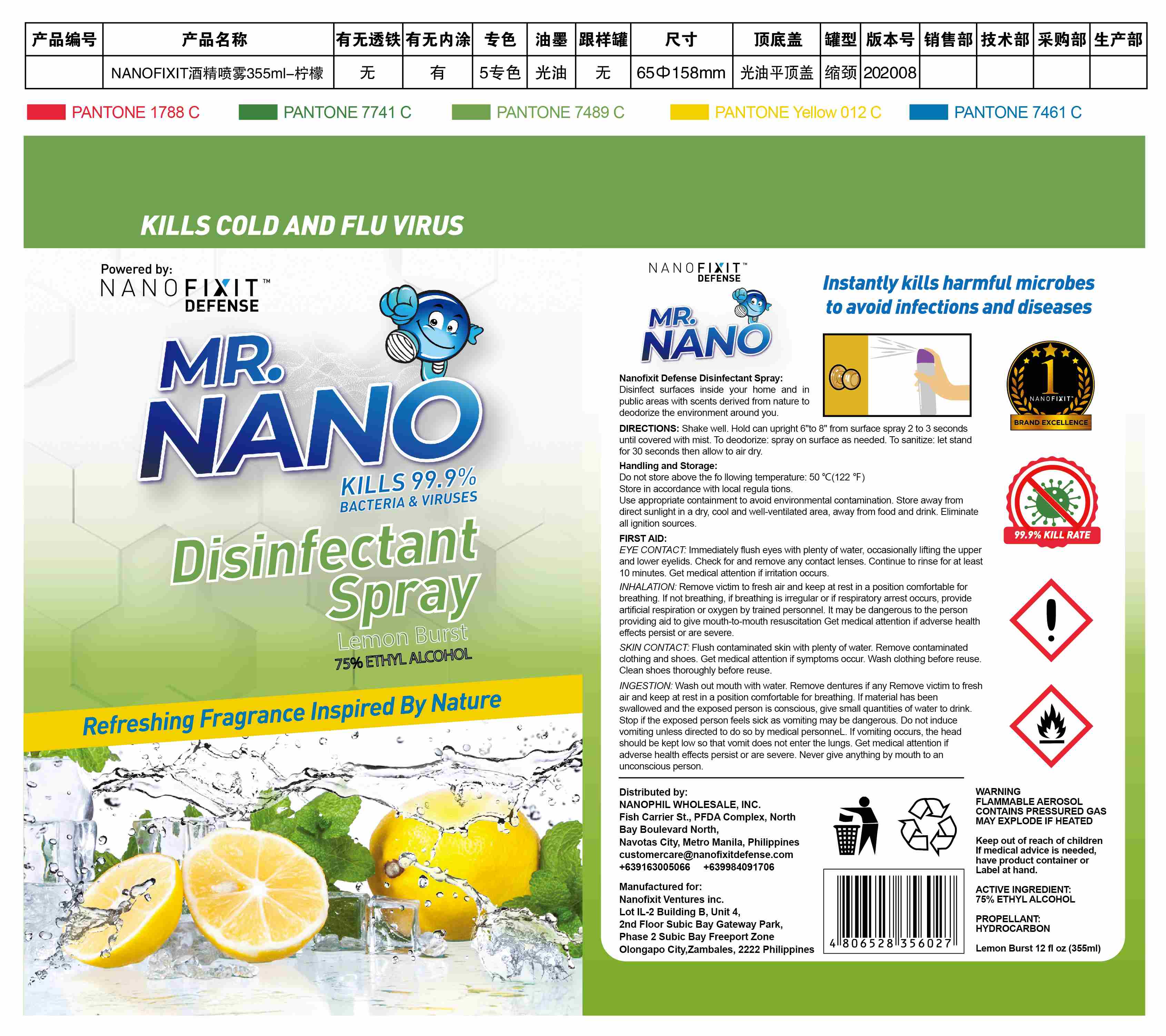 DRUG LABEL: Disinfectant
NDC: 92763-008 | Form: SPRAY
Manufacturer: NANOFIXIT VENTURES INC.
Category: otc | Type: HUMAN OTC DRUG LABEL
Date: 20200904

ACTIVE INGREDIENTS: ALCOHOL 141.5 g/355 mL
INACTIVE INGREDIENTS: BUTANE; SODIUM BENZOATE; TROLAMINE; FRAGRANCE LAVENDER & CHIA F-153480; WATER; PROPANE; ISOBUTANE

DOSAGE AND ADMINISTRATION

Do not store above the following temperature: 50°C [122°F) Store in accordance with local regulations.Use appropriate containment to avoid environmental contamination.Store away from direct sunlight in a dry, cool and well-ventilated area, away from food and drink. Eliminate all ignition sources.

INACTIVE INGREDIENT

Water

Butane

Propane

Isobutane

Sodium benzoate

Triethanolamine

Parfum（LEMON）

INDICATIONS AND USAGE

Shake well. Hold can upright 6" to 8”from surface. Spray 2 to 3 seconds until covered with mist.

To deodorize: spray on surface as needed.

To sanitize: let stand for 30 seconds then allow to air dry.

ACTIVE INGREDIENT

Ethanol

keep out of reach of children

PURPOSE

Disinfection
Sterilization
No Rinseing

WARNINGS

FLAMMABLE AEROSOL CONTAINS PRESSURED GAS MAY EXPLODE IF HEATED